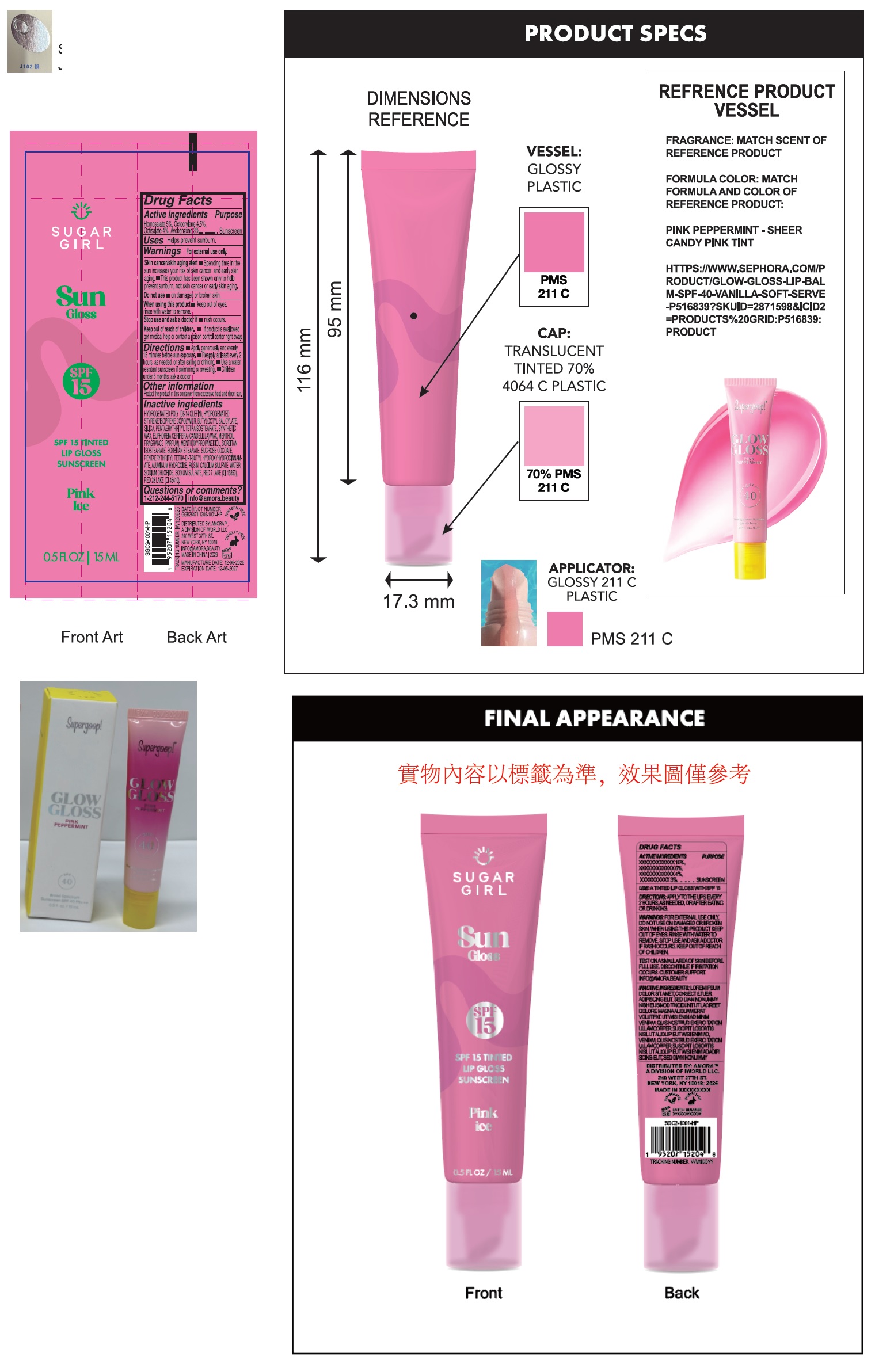 DRUG LABEL: Sugargirl Sun Gloss SPF 15 Tinted Lip Gloss Sunscreen Pink Ice
NDC: 85179-044 | Form: LIQUID
Manufacturer: I World LLC
Category: otc | Type: HUMAN OTC DRUG LABEL
Date: 20260127

ACTIVE INGREDIENTS: HOMOSALATE 50 mg/1 mL; OCTOCRYLENE 45 mg/1 mL; OCTISALATE 40 mg/1 mL; AVOBENZONE 30 mg/1 mL
INACTIVE INGREDIENTS: BUTYLOCTYL SALICYLATE; SILICON DIOXIDE; PENTAERYTHRITYL TETRAISOSTEARATE; EUPHORBIA CERIFERA (CANDELILLA) WAX; MENTHOL, UNSPECIFIED FORM; 3-((L-MENTHYL)OXY)PROPANE-1,2-DIOL; SORBITAN ISOSTEARATE; SORBITAN MONOSTEARATE; SUCROSE COCOATE; PENTAERYTHRITOL TETRAKIS(3-(3,5-DI-TERT-BUTYL-4-HYDROXYPHENYL)PROPIONATE); ALUMINUM HYDROXIDE; ROSIN; CALCIUM SULFATE; WATER; SODIUM CHLORIDE; SODIUM SULFATE; D&C RED NO. 6; D&C RED NO. 28

Sugargirl Sun Gloss SPF 15 Tinted Lip Gloss Sunscreen Pink Ice

Active ingredients

Homosalate 5%, Octocrylene 4.5%, Octisalate 4%, Avobenzone 3%

Purpose

Sunscreen

Uses

- Helps prevent sunburn.

Warnings

For external use only.
Skin cancer/skin aging alert

- Spending time in the sun increases your risk of skin cancer and early skin aging.
- This product has been shown only to help prevent sunburn, notskin cancer or early skin aging.

Do not use

- on damaged or broken skin.

when using this product

- keep out of eyes. rinse with water to remove.

Stop use and ask a doctor if

- rash occurs.

Keep out of reach of children.

- If product is swallowed get medical help or contact a poison control centre right away.

Directions

- Apply generously and evenly 15 minutes before sun exposer.
- Reapply at least every 2 hours.
- Use a water resistant sunscreen if swimming or sweating.
- Children under 6 month: ask a doctor.

Other information

Protect the product in this container from excessive heat and direct sun.

Inactive ingredients

HYDROGENATED POLY (C6-14 OLEFIN), HYDROGENATED STYRENE/ISOPRENE COPOLYMER, BUTYLOCTYL SALICYLATE, SILICA, PENTAERYTHRITYL TETRAISOSTEARATE, SYNTHETIC WAX, EUPHORBIA CERIFERA (CANDELILLA) WAX, MENTHOL, FRAGRANCE (PARFUM), MENTHOXYPROPANEDIOL, SORBITAN ISOSTEARATE, SORBITAN STEARATE, SUCROSE COCOATE, PENTAERYTHRITYL TETRA-DI-T-BUTYL HYDROXYHYDROCINNAMATE, ALUMINUM HYDROXIDE, ROSIN, CALCIUM SULFATE, WATER, SODIUM CHLORIDE, SODIUM SULFATE, RED 7 LAKE (CI 15850), RED 28 LAKE (CI 45410).

Questions or comments?

1-212-244-5170 info@amora.beauty